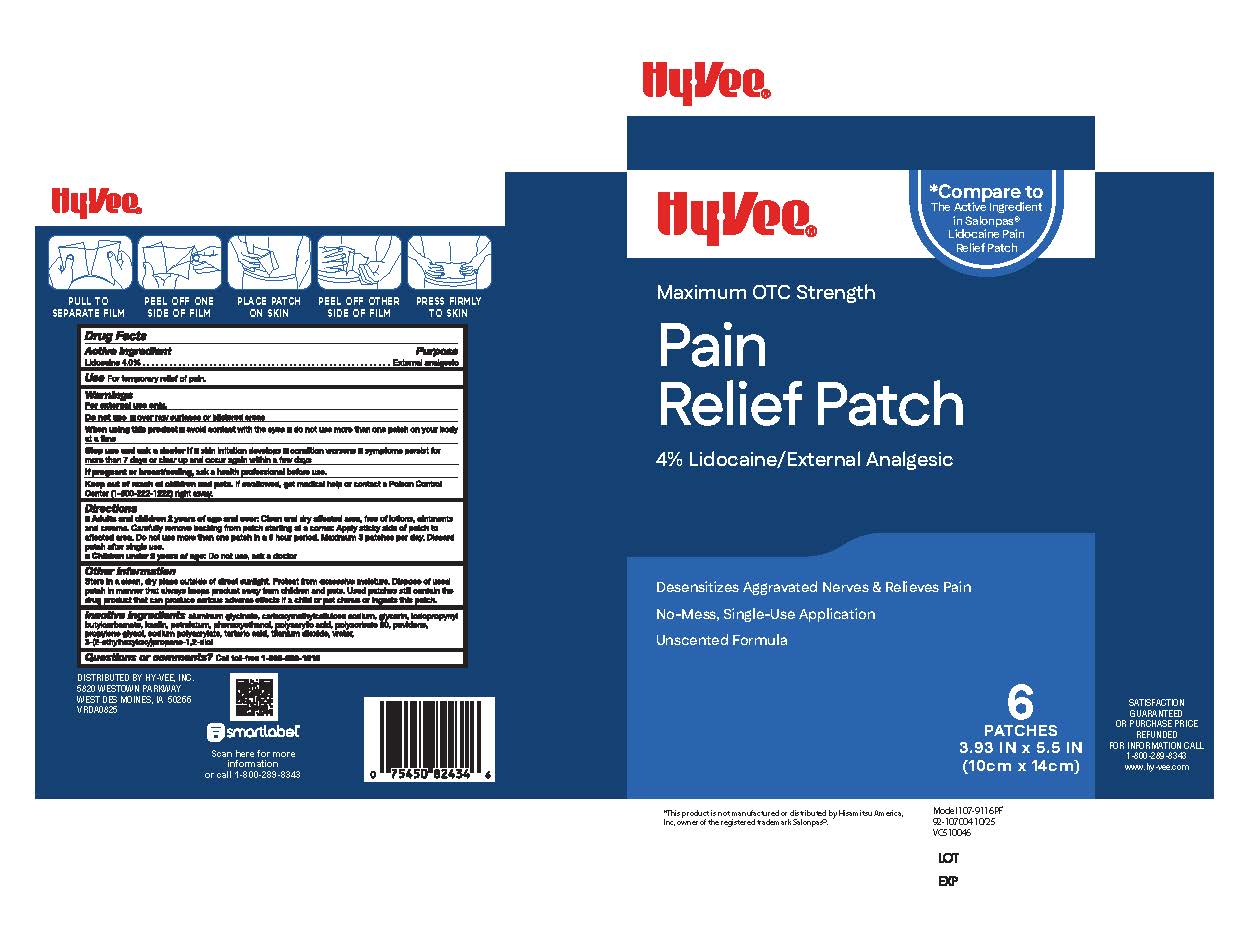 DRUG LABEL: Pain Relief Patch Lidocaine
NDC: 42507-960 | Form: PATCH
Manufacturer: HyVee
Category: otc | Type: HUMAN OTC DRUG LABEL
Date: 20251117

ACTIVE INGREDIENTS: LIDOCAINE 4 g/100 g
INACTIVE INGREDIENTS: SODIUM POLYACRYLATE (2500000 MW); POVIDONE, UNSPECIFIED; DIHYDROXYALUMINUM AMINOACETATE; POLYACRYLIC ACID (8000 MW); POLYSORBATE 80; KAOLIN; GLYCERIN; ETHYLHEXYLGLYCERIN; PROPYLENE GLYCOL; PHENOXYETHANOL; TARTARIC ACID; TITANIUM DIOXIDE; WATER; IODOPROPYNYL BUTYLCARBAMATE; CARBOXYMETHYLCELLULOSE SODIUM, UNSPECIFIED FORM; PETROLATUM

Pain Relief Patch 4% Lidocaine

Active Ingredient

Lidocaine 4%

Purpose

External analgesic

Uses

For temporary relief of pain

Warnings

For external use only

Do not use

over raw surfeces or blistered areas

When using this product

■ avoid contact with the eyes

■ do not use more than one patch on your body at a time

Stop use and ask a doctor if

skin irritation develops
conditions worsen
symptoms persist for more than 7 days or clear up and occur again within a few days

If pregnant or breast-feeding,

ask a health professional before use.

Keep out of reach of children and pets.

If swallowed, get medical help or contact a Poison Control Center 800-222-1222 right away.

Directions

■ Adults and children 2 years of age and over: Clean and dry affected area, free of lotions, ointments and creams. Carefully remove backing from patch starting at a corner. Apply sticky side of patch to affected area. Do not use more than one patch in a 8 hour period. Maximum 3 patches per day. Discard patch after single use.

■Children under 2 years of age: Do not use, ask a doctor

Other information

Store in a clean, dry place outside of direct sunlight. Protect from excessive moisture. Dispose of used patch in manner that always keeps product away from children and pets. Used patches still contain the drug product that can produce serious adverse effects if a child or pet chews or ingests this patch.

Inactive Ingredients

aluminum glycinate, carboxymethylcellulose sodium, glycerin, iodopropynyl butylcarbamate, kaolin, petrolatum, phenoxyethanol, polyacrylic acid, polysorbate 80, povidone, propylene glycol, sodium polyacrylate, tartaric acid, titanium dioxide, water, 3-(2-ethylhexyloxy)propane-1,2-diol

Questions or comments?

Toll free 866-326-1313